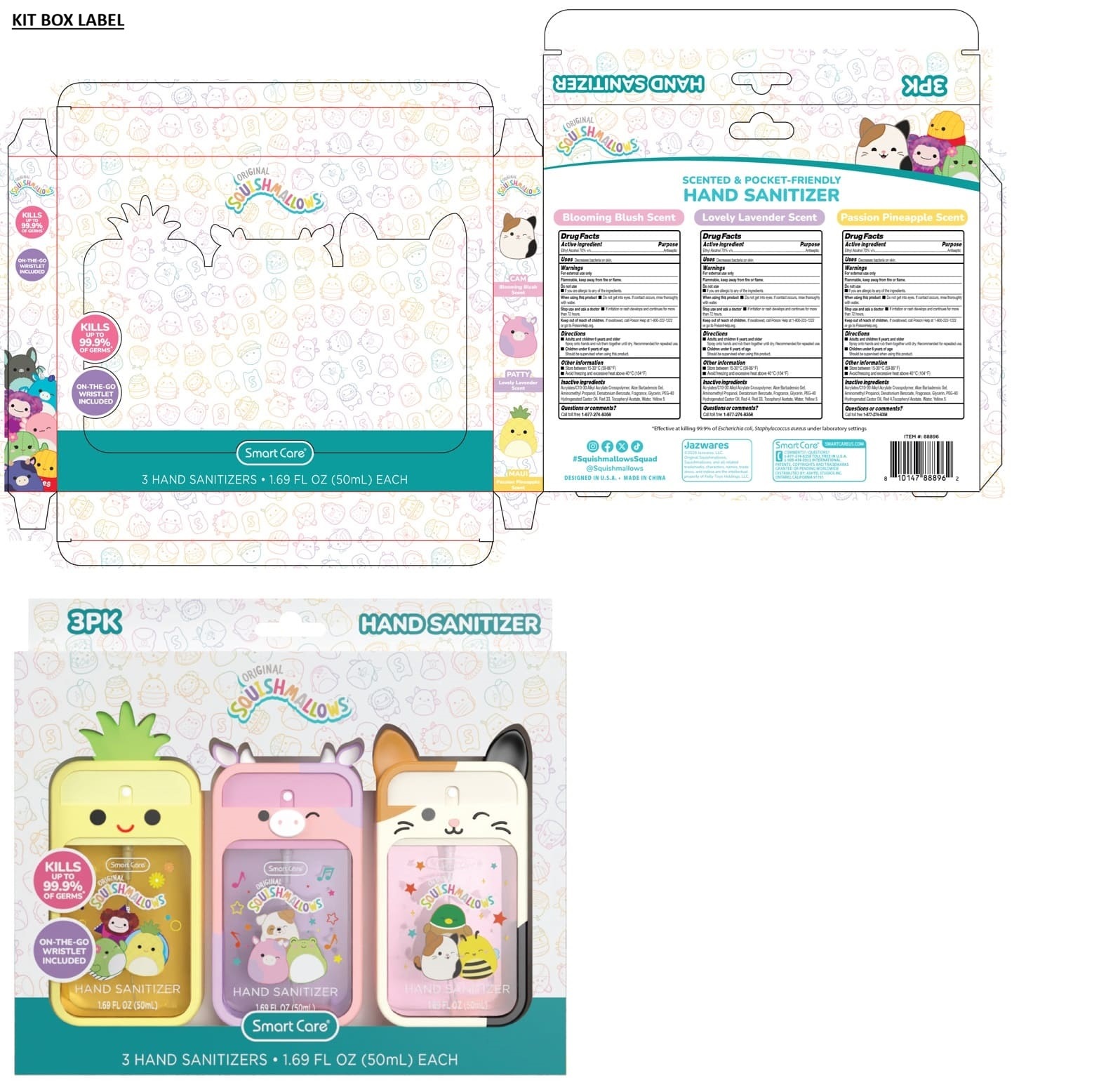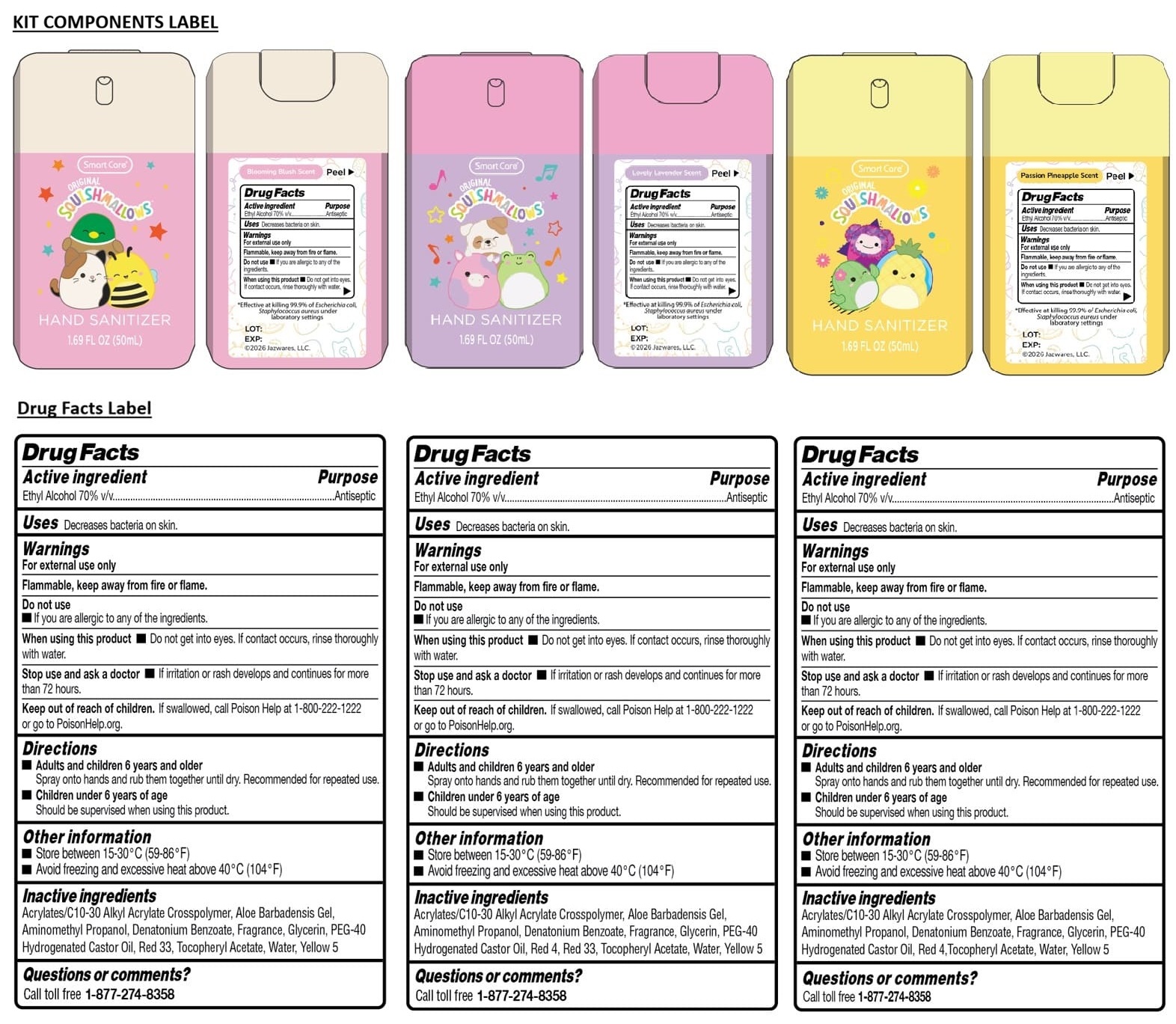 DRUG LABEL: Smart Care SQUISHMALLOWS 1.69 FL OZ 3PK HAND SANITIZERS (Blooming Blush Scent, Lovely Lavender Scent, Passion Pineapple Scent)
NDC: 70108-289 | Form: KIT | Route: TOPICAL
Manufacturer: Ashtel Studios, Inc.
Category: otc | Type: HUMAN OTC DRUG LABEL
Date: 20260113

ACTIVE INGREDIENTS: ALCOHOL 70 mL/100 mL; ALCOHOL 70 mL/100 mL; ALCOHOL 70 mL/100 mL
INACTIVE INGREDIENTS: ACRYLATES/C10-30 ALKYL ACRYLATE CROSSPOLYMER (60000 MPA.S); ALOE VERA LEAF; AMINOMETHYLPROPANOL; DENATONIUM BENZOATE; GLYCERIN; POLYOXYL 40 HYDROGENATED CASTOR OIL; D&C RED NO. 33; .ALPHA.-TOCOPHEROL ACETATE; WATER; FD&C YELLOW NO. 5; ACRYLATES/C10-30 ALKYL ACRYLATE CROSSPOLYMER (60000 MPA.S); ALOE VERA LEAF; AMINOMETHYLPROPANOL; DENATONIUM BENZOATE; GLYCERIN; POLYOXYL 40 HYDROGENATED CASTOR OIL; FD&C RED NO. 4; D&C RED NO. 33; .ALPHA.-TOCOPHEROL ACETATE; WATER; FD&C YELLOW NO. 5; ACRYLATES/C10-30 ALKYL ACRYLATE CROSSPOLYMER (60000 MPA.S); ALOE VERA LEAF; AMINOMETHYLPROPANOL; DENATONIUM BENZOATE; GLYCERIN; POLYOXYL 40 HYDROGENATED CASTOR OIL; FD&C RED NO. 4; .ALPHA.-TOCOPHEROL ACETATE; WATER; FD&C YELLOW NO. 5

Smart Care® SQUISHMALLOWS 1.69 FL OZ 3PK HAND SANITIZERS (Blooming Blush Scent, Lovely Lavender Scent, Passion Pineapple Scent)

Smart Care HAND SANITIZER Blooming Blush Scent

Drug Facts

Active ingredient

Ethyl Alcohol 70% v/v

Purpose

Antiseptic

Uses

Decreases bacteria on skin.

Warnings

For external use only

Flammable, keep away from fire or flame.

Do not use
• If you are allergic to any of the ingredients.

When using this product • Do not get into eyes. If contact occurs, rinse thoroughly with water.

Stop use and ask a doctor • If irritation or rash develops and continues for more than 72 hours.

Keep out of reach of children. If swallowed, call Poison Help at 1-800-222-1222 or go to Poisonhelp.org.

Directions

• Adults and children 6 years and older
Spray onto hands and rub them together until dry. Recommended for repeated use.

• Children under 6 years of age
Should be supervised when using this product.

Other information

• Store between 15-30°C (59-86°F)
• Avoid freezing and excessive heat above 40°C (104°F)

Inactive ingredients

Acrylates/C10-30 Alkyl Acrylate Crosspolymer, Aloe Barbadensis Gel, Aminomethyl Propanol, Denatonium Benzoate, Fragrance, Glycerin, PEF-40 Hydrogenated Castor Oil, Red 33, Tocopheryl Acetate, Water, Yellow 5

Questions or comments?

Call toll free 1-877-274-8358

Smart Care HAND SANITIZER Lovely Lavender Scent

Drug Facts

Active ingredient

Ethyl Alcohol 70% v/v

Purpose

Antiseptic

Uses

Decreases bacteria on skin.

Warnings

For external use only

Flammable, keep away from fire or flame.

Do not use
• If you are allergic to any of the ingredients.

When using this product • Do not get into eyes. If contact occurs, rinse thoroughly with water.

Stop use and ask a doctor • If irritation or rash develops and continues for more than 72 hours.

Keep out of reach of children. If swallowed, call Poison Help at 1-800-222-1222 or go to Poisonhelp.org.

Directions

• Adults and children 6 years and older
Spray onto hands and rub them together until dry. Recommended for repeated use.

• Children under 6 years of age
Should be supervised when using this product.

Other information

• Store between 15-30°C (59-86°F)
• Avoid freezing and excessive heat above 40°C (104°F)

Inactive ingredients

Acrylates/C10-30 Alkyl Acrylate Crosspolymer, Aloe Barbadensis Gel, Aminomethyl Propanol, Denatonium Benzoate, Fragrance, Glycerin, PEF-40 Hydrogenated Castor Oil, Red 4, Red 33, Tocopheryl Acetate, Water, Yellow 5

Questions or comments?

Call toll free 1-877-274-8358

Smart Care HAND SANITIZER Passion Pineapple Scent

Drug Facts

Active ingredient

Ethyl Alcohol 70% v/v

Purpose

Antiseptic

Uses

Decreases bacteria on skin.

Warnings

For external use only

Flammable, keep away from fire or flame.

Do not use
• If you are allergic to any of the ingredients.

When using this product • Do not get into eyes. If contact occurs, rinse thoroughly with water.

Stop use and ask a doctor • If irritation or rash develops and continues for more than 72 hours.

Keep out of reach of children. If swallowed, call Poison Help at 1-800-222-1222 or go to Poisonhelp.org.

Directions

• Adults and children 6 years and older
Spray onto hands and rub them together until dry. Recommended for repeated use.

• Children under 6 years of age
Should be supervised when using this product.

Other information

• Store between 15-30°C (59-86°F)
• Avoid freezing and excessive heat above 40°C (104°F)

Inactive ingredients

Acrylates/C10-30 Alkyl Acrylate Crosspolymer, Aloe Barbadensis Gel, Aminomethyl Propanol, Denatonium Benzoate, Fragrance, Glycerin, PEF-40 Hydrogenated Castor Oil, Red 4, Tocopheryl Acetate, Water, Yellow 5

Questions or comments?

Call toll free 1-877-274-8358

ORIGINAL

KILLS UP TO 99.9% OF GERMS*

ON-THE-GO WRISTLET INCLUDED

Blooming Blush Scent
CAM

Lovely Lavender Scent
PATTY

Passion Pineapple Scent
MAUI

SCENTED & POCKET-FRIENDLY

*Effective at killing 99.9% of Escherichia Coli, Staphylococcus aureus under laboratory settings

#SquishmallowsSquad

@Squishmallows

DESIGNED IN U.S.A. • MADE IN CHINA

Jazwares™
©2026 Jazwares, LLC.
Original Squishmallows, Squishmallows, and all related trademarks, characters, names, trade dress, and indicia are the intellectual property of Kelly Toys Holdings, LLC.

SmartCare® SMARTCAREUS.COM

1-909-434-0911 INTERNATIONAL

PATENTS, COPYRIGHTS AND TRADEMARKS GRANTED OR PENDING WORLDWIDE

DISTRIBUTED BY: ASHTEL STUDIOS INC.
ONTARIO, CALIFORNIA 91761